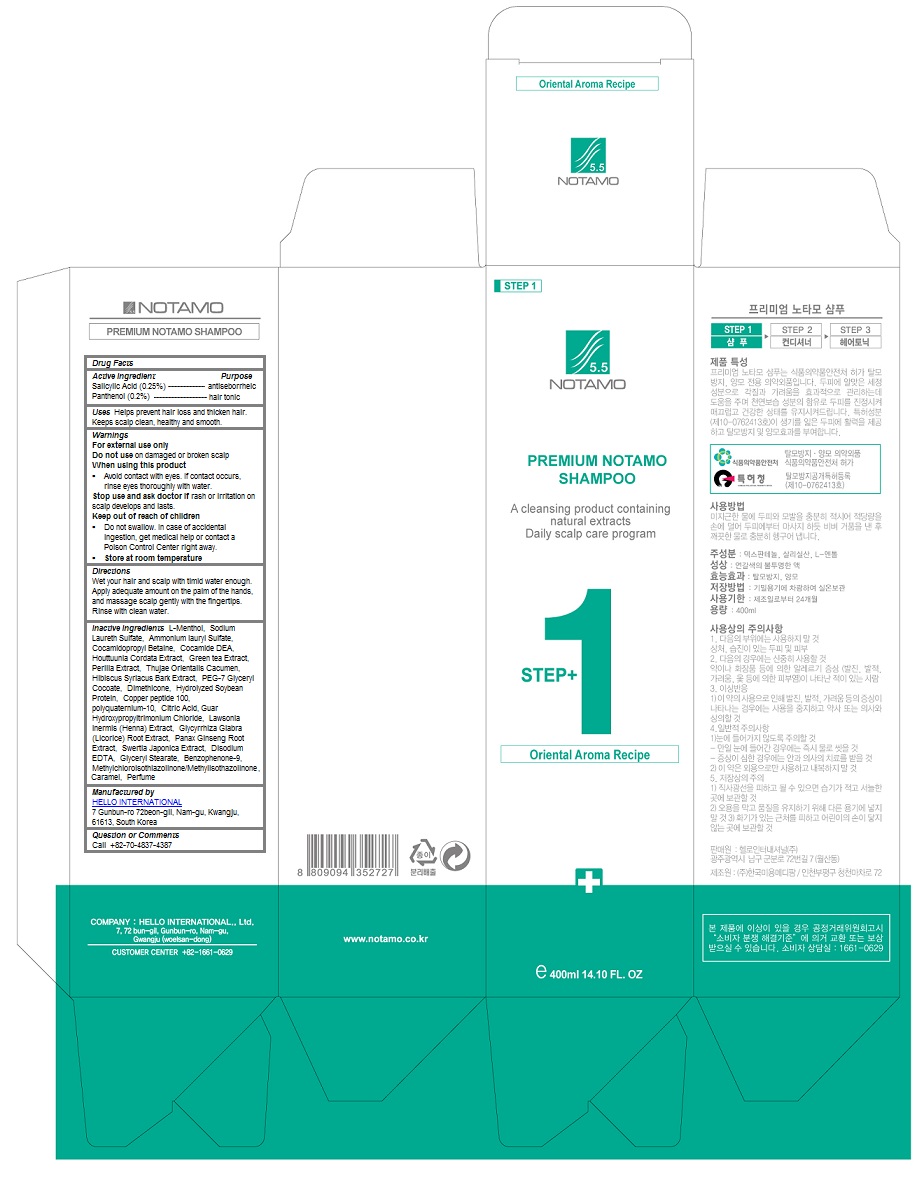 DRUG LABEL: Premium Notamo
NDC: 69709-103 | Form: SHAMPOO
Manufacturer: HELLO INTERNATIONAL
Category: otc | Type: HUMAN OTC DRUG LABEL
Date: 20160307

ACTIVE INGREDIENTS: PANTHENOL 0.002 1/400 mL; SALICYLIC ACID 0.0025 1/400 mL
INACTIVE INGREDIENTS: LEVOMENTHOL; SODIUM LAURETH-3 SULFATE; AMMONIUM LAURYL SULFATE; COCAMIDOPROPYL BETAINE; COCO DIETHANOLAMIDE; HOUTTUYNIA CORDATA FLOWERING TOP; GREEN TEA LEAF; HIBISCUS SYRIACUS BARK; PEG-7 GLYCERYL COCOATE; Dimethicone; POLYQUATERNIUM-10 (1000 MPA.S AT 2%); CITRIC ACID MONOHYDRATE; GUAR HYDROXYPROPYLTRIMONIUM CHLORIDE (1.7 SUBSTITUENTS PER SACCHARIDE); GLYCYRRHIZA GLABRA; ASIAN GINSENG; SWERTIA JAPONICA WHOLE FLOWERING; EDETATE DISODIUM; GLYCERYL MONOSTEARATE; Benzophenone-9; Caramel

Premium Notamo Shampoo